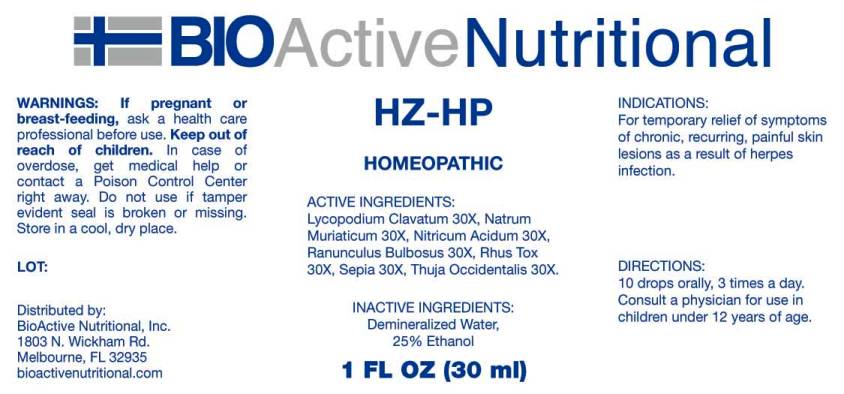 DRUG LABEL: HZ
NDC: 43857-0152 | Form: LIQUID
Manufacturer: BioActive Nutritional, Inc.
Category: homeopathic | Type: HUMAN OTC DRUG LABEL
Date: 20160719

ACTIVE INGREDIENTS: LYCOPODIUM CLAVATUM SPORE 30 [hp_X]/1 mL; SODIUM CHLORIDE 30 [hp_X]/1 mL; NITRIC ACID 30 [hp_X]/1 mL; RANUNCULUS BULBOSUS 30 [hp_X]/1 mL; TOXICODENDRON PUBESCENS LEAF 30 [hp_X]/1 mL; SEPIA OFFICINALIS JUICE 30 [hp_X]/1 mL; THUJA OCCIDENTALIS LEAF 30 [hp_X]/1 mL
INACTIVE INGREDIENTS: WATER; ALCOHOL

Drug Facts:

ACTIVE INGREDIENTS:

Lycopodium Clavatum 30X, Natrum Muriaticum 30X, Nitricum Acidum 30X, Ranunculus Bulbosus 30X, Rhus Tox 30X, Sepia 30X, Thuja Occidentalis 30X.

INDICATIONS:

For temporary relief of symptoms of chronic, recurring, painful skin lesions as a result of herpes infection.

WARNINGS:

If pregnant or breast-feeding, ask a health care professional before use.

Keep out of reach of children. In case of overdose, get medical help or contact a Poison Control Center right away.

Do not use if tamper evident seal is broken or missing.

Store in cool, dry place.

DIRECTIONS:

10 drops orally, 3 times a day. Consult a physician for use in children under 12 years of age.

INACTIVE INGREDIENTS:

Demineralized Water, 25% Ethanol.

Keep out of reach of children. In case of overdose, get medical help or contact a Poison Control Center right away.

INDICATIONS:

For temporary relief of symptoms of chronic, recurring, painful skin lesions as a result of herpes infection.

QUESTIONS:

Distributed by:
BioActive Nutritional, Inc.
1803 N. Wickham Rd.
Melbourne, FL 32935
bioactivenutritional.com

PACKAGE LABEL DISPLAY:

BIOActive Nutritional

HZ-HP

HOMEOPATHIC

1 FL OZ (30 ml)